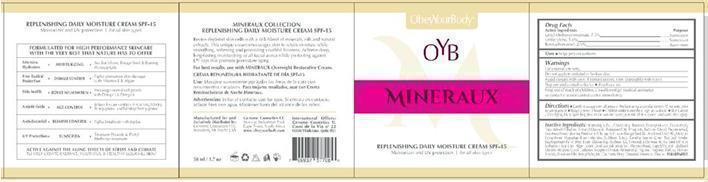 DRUG LABEL: REVITALIZING MOISTURIZING Sunscreen SPF 20
NDC: 61791-126 | Form: CREAM
Manufacturer: GENOME COSMETICS, LLC
Category: otc | Type: HUMAN OTC DRUG LABEL
Date: 20131022

ACTIVE INGREDIENTS: OCTOCRYLENE 10 g/100 g; OCTINOXATE 7.5 g/100 g; AVOBENZONE 3.0 g/100 g
INACTIVE INGREDIENTS: WATER; SUNFLOWER OIL; CETOSTEARYL ALCOHOL; LIMNANTHES ALBA WHOLE; SAFFLOWER OIL; MEADOWFOAM SEED OIL FATTY ACIDS; POLYSORBATE 60; CRAMBE HISPANICA SUBSP. ABYSSINICA SEED OIL; JOJOBA OIL; MEADOWLACTONE; OLIVE OIL; POLYOXYL 40 HYDROGENATED CASTOR OIL; MEADOWFOAMAMIDOPROPYL BETAINE; STEARETH-20; POLYSORBATE 65; PHENOXYETHANOL; CARBOMER 940; PANTHENOL; .BETA.-SITOSTEROL; AMINOMETHYLPROPANOL; FD&C YELLOW NO. 6; .ALPHA.-TOCOPHEROL ACETATE; CAPRYLYL GLYCOL; ETHYLHEXYLGLYCERIN; HEXYLENE GLYCOL; CHOLECALCIFEROL; CALENDULA OFFICINALIS FLOWER; CHAMAEMELUM NOBILE FLOWER; TRIPEPTIDE-10 CITRULLINE; UBIDECARENONE; SEA SALT; GLYCINE; SOYBEAN OIL; EVENING PRIMROSE OIL; BORAGE OIL; ALOE VERA LEAF; NORI; HIPPOPHAE RHAMNOIDES FRUIT JUICE

REVITALIZING MOISTURIZING SUNSCREEN CREAM - SPF-20

Active ingredient

OCTOCRYLENE 10.0%

OCTINOXATE 7.5%

AVOBENZONE 3.0%

Purpose

Sunscreen

Uses

- helps prevent sunburn

Warnings

For external use only.

Do not apply to

- irritated or broken skin.

Warnings

Consult a doctor

- Stop use and consult a doctor if rash occurs.

Warnings

Stop use

- Stop use and consult a doctor if rash occurs

Keep Out of Reach of Children.

If swallowed, get medical help or contact a Poison Control Center right away.

Directions

- Gently massage onto all areas of the face using a circular motion 15 minutes prior
  to sun exposure
- Reapply every two hours
- For children under 6 months of age, ask a doctor
- Skin Cancer/Skin Aging Alert: Spending time in the sun increases your risk of skin cancer and early skin aging.

Other Information

- protect the product in this container from excessive heat and direct sun

Inactive Ingredients

Water (AQUA, EAU), Helianthus Annuus Seed Oil, Cetearyl Alcohol, Limnanthes Alba, Carthamus Tinctorius (SAFFLOWER) Seed Oil, Meadowfoam Estolide, Polysorbate-60, Crambe Abyssinica Seed Oil, Simmondsia Chinesis (JOJOBA) Seed Oil, Meadowfoam Delta-Lactone, Olea Europaea (OLIVE) Oil Unsaponifiables, PEG-40 Hydrogenated Castor Oil, Meadowfoamamidopropyl Betaine, Dimethicone PEG-8 Meadowfoamate, Steareth-20, Polysorbate-65, Phenoxyethanol, Carbomer, Panthenol, Phytosterol, Aminomethylpropanol, CI15985 (YELLOW 6), Tocopheryl Acetate, Fragrance (Parfum), Caprylyl Glycol, Ethylhexylglycerin, Hexylene Glycol, Cholecalciferol, Calendula Officinalis Flower Extract, Anthemis Nobilis (CHAMOMILE) Flower Extract, Beta Sitosterol, Tripeptide-10 Citrulline, Ubiquinone Q10, Sea Salt, Glycine Soja (Soybean) Oil, Oenothera Biennis (EVENING PRIMROSE) Oil (OMEGA-3), Borago Officinalis (BORAGE) Seed Oil (OMEGA-6), Aloe Barbadensis Leaf Juice, Algae Extract, Hippophae Rhamnoides (SEA BUCKTHORN) Extract. PARABEN-FREE

Package/Label Principal Display Panel

DARK & BEAUTY REVITALIZING MOISTURIZING CREAM SPF-20

Manufactured for and exclusively distributed by:

Genome Cosmetics LLC

Bensalem, PA 19020 USA

Made in the U.S.A

Carton Label